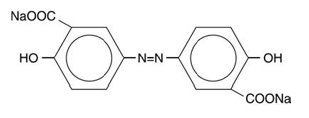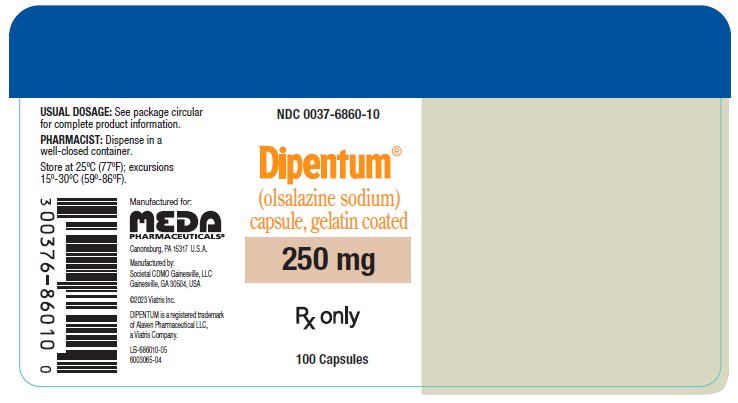 DRUG LABEL: Dipentum
NDC: 0037-6860 | Form: CAPSULE, GELATIN COATED
Manufacturer: Viatris Specialty LLC
Category: prescription | Type: HUMAN PRESCRIPTION DRUG LABEL
Date: 20240718

ACTIVE INGREDIENTS: OLSALAZINE SODIUM 250 mg/1 1
INACTIVE INGREDIENTS: MAGNESIUM STEARATE; FERROSOFERRIC OXIDE; CARAMEL; GELATIN, UNSPECIFIED; TITANIUM DIOXIDE

HIGHLIGHTS OF PRESCRIBING INFORMATION

These highlights do not include all the information needed to use DIPENTUM safely and effectively. See full prescribing information for DIPENTUM.
DIPENTUM (olsalazine sodium) capsules, for oral use
Initial U.S. Approval: 1987

1 INDICATIONS AND USAGE

DIPENTUM is an aminosalicylate indicated for the maintenance of remission of ulcerative colitis in adult patients who are intolerant of sulfasalazine. (1)

2 DOSAGE AND ADMINISTRATION

- Evaluate renal function prior to initiation of DIPENTUM and periodically while on therapy. (2, 5.1)
- The recommended dosage is 500 mg orally twice daily. (2)
- Drink an adequate amount of fluids. (2, 5.7)

3 DOSAGE FORMS AND STRENGTHS

Capsules: 250 mg olsalazine sodium (3)

4 CONTRAINDICATIONS

Known or suspected hypersensitivity to salicylates or aminosalicylates or to any of the ingredients of DIPENTUM. (4, 5.3)

5 WARNINGS AND PRECAUTIONS

- Renal Impairment: Assess renal function at the beginning of treatment and periodically during treatment. Discontinue DIPENTUM if renal function deteriorates while on therapy. (5.1, 7.1)
- Mesalamine-Induced Acute Intolerance Syndrome: Discontinue treatment if acute intolerance syndrome (cramping, acute abdominal pain, bloody diarrhea, sometimes fever, headache and rash) is suspected. (5.2)
- Hypersensitivity Reactions, including myocarditis and pericarditis: Discontinue DIPENTUM if a hypersensitivity reaction is suspected. (5.3)
- Hepatic Failure: Evaluate the risks and benefits of using DIPENTUM in patients with known liver impairment. (5.4)
- Severe Cutaneous Adverse Reactions: Discontinue at the first signs or symptoms of severe cutaneous adverse reactions or other signs of hypersensitivity and consider further evaluation. (5.5)
- Photosensitivity: Avoid sun exposure if pre-existing skin conditions. (5.6)
- Nephrolithiasis: Cases of nephrolithiasis have been reported with the use of mesalamine. Mesalamine-containing stones are undetectable by standard radiography or computed tomography (CT). Ensure adequate hydration during treatment. (5.7)
- Interference with Laboratory Tests: Mesalamine may lead to elevated urinary normetanephrine test results. (5.8)

6 ADVERSE REACTIONS

Most common adverse reactions (≥2%) are: diarrhea, abdominal pain/cramps, nausea, arthralgia/joint pain, rash, upper respiratory infection and depression. (6)

To report SUSPECTED ADVERSE REACTIONS, contact Meda Pharmaceuticals Inc. at 1-888-380-3276 or FDA at 1-800-FDA-1088 or www.fda.gov/medwatch.

7 DRUG INTERACTIONS

- Nephrotoxic Agents including Non-Steroidal Anti-inflammatory Drugs (NSAIDs): Increased risk of nephrotoxicity; monitor for changes in renal function and mesalamine-related adverse reactions. (7.1)
- Azathioprine or 6-Mercaptopurine: Increased risk of blood dyscrasias; monitor complete blood cell counts and platelet counts. (7.2)
- Low Molecular Weight Heparins or Heparinoids: Increased risk of bleeding following neuraxial anesthesia; if possible, discontinue DIPENTUM or closely monitor for bleeding. (7.1)
- Varicella Vaccine: Avoid use for 6 weeks after vaccination. (7.4)

8 USE IN SPECIFIC POPULATIONS

Geriatric Patients: Increased risk of blood dyscrasias; monitor complete blood cell counts and platelet counts. (8.5)

FULL PRESCRIBING INFORMATION

1 INDICATIONS AND USAGE

DIPENTUM is indicated for the maintenance of remission of ulcerative colitis in adult patients who are intolerant of sulfasalazine.

2 DOSAGE AND ADMINISTRATION

Evaluate renal function before initiating therapy with DIPENTUM [see Warnings and Precautions (5.1)].

The recommended dosage is 500 mg orally twice daily.

Drink an adequate amount of fluids during treatment [see Warnings and Precautions (5.7)].

3 DOSAGE FORMS AND STRENGTHS

Capsules: 250 mg olsalazine sodium in beige capsules imprinted with DIPENTUM® 250 mg on the capsule shell

4 CONTRAINDICATIONS

DIPENTUM is contraindicated in patients with known or suspected hypersensitivity to salicylates, aminosalicylates, or to any of the excipients in DIPENTUM [see Warnings and Precautions (5.3), Description (11)].

5 WARNINGS AND PRECAUTIONS

5.1 Renal Impairment

Renal impairment, including minimal change disease, acute and chronic interstitial nephritis, and renal failure have been reported in patients given DIPENTUM or other products that contain mesalamine or are converted to mesalamine. In animal studies, the kidney was the principal organ of mesalamine toxicity [see Nonclinical Toxicology (13.2)].

Evaluate the risks and benefits of using DIPENTUM in patients with known renal impairment or a history of renal disease or taking concomitant nephrotoxic drugs. Evaluate renal function in all patients prior to initiation and periodically while on DIPENTUM therapy. Discontinue DIPENTUM if renal function deteriorates while on therapy [see Drug Interactions (7.1), Use in Specific Populations (8.6)].

5.2 Mesalamine-Induced Acute Intolerance Syndrome

Olsalazine is converted to mesalamine, which has been associated with an acute intolerance syndrome that may be difficult to distinguish from an exacerbation of ulcerative colitis. Symptoms include cramping, acute abdominal pain and bloody diarrhea, sometimes fever, headache, and rash. Monitor patients for worsening of these symptoms while on treatment. If acute intolerance syndrome is suspected, promptly discontinue treatment with DIPENTUM.

5.3 Hypersensitivity Reactions

Some patients who have experienced a hypersensitivity reaction to sulfasalazine may have a similar reaction to DIPENTUM or to other compounds that contain or are converted to mesalamine. Mesalamine‑induced hypersensitivity reactions may present as internal organ involvement, including myocarditis, pericarditis, nephritis, hepatitis, pneumonitis, and hematologic abnormalities. Evaluate patients immediately if signs or symptoms of a hypersensitivity reaction are present. Discontinue DIPENTUM if an alternative etiology for the signs and symptoms cannot be established.

5.4 Hepatic Failure

There have been reports of hepatic failure in patients with pre-existing liver disease who have been administered mesalamine. Because olsalazine is converted to mesalamine, evaluate the risks and benefits of using DIPENTUM in patients with known liver impairment.

5.5 Severe Cutaneous Adverse Reactions

Severe cutaneous adverse reactions, including Stevens-Johnson syndrome (SJS) and toxic epidermal necrolysis (TEN), drug reaction with eosinophilia and systemic symptoms (DRESS), and acute generalized exanthematous pustulosis (AGEP) have been reported with the use of mesalamine, the active moiety in DIPENTUM [see Adverse Reactions (6.2)]. Discontinue DIPENTUM at the first signs or symptoms of severe cutaneous adverse reactions or other signs of hypersensitivity and consider further evaluation.

5.6 Photosensitivity

Patients with pre‑existing skin conditions such as atopic dermatitis and atopic eczema have reported more severe photosensitivity reactions. Advise patients to avoid sun exposure, wear protective clothing, and use a broad-spectrum sunscreen when outdoors.

5.7 Nephrolithiasis

Cases of nephrolithiasis have been reported with the use of mesalamine, the active moiety in DIPENTUM, including stones with 100% mesalamine content. Mesalamine‑containing stones are radiotransparent and undetectable by standard radiography or computed tomography (CT). Ensure adequate fluid intake during treatment.

5.8 Interference with Laboratory Tests

Use of DIPENTUM, which is converted to mesalamine, may lead to spuriously elevated test results when measuring urinary normetanephrine by liquid chromatography with electrochemical detection because of the similarity in the chromatograms of normetanephrine and the main metabolite of mesalamine, N‑acetyl‑5‑aminosalicylic acid (N‑Ac‑5‑ASA). Consider an alternative, selective assay for normetanephrine.

6 ADVERSE REACTIONS

The following clinically significant adverse reactions are described elsewhere in the labeling:

- Renal impairment [see Warnings and Precautions (5.1)]
- Mesalamine-induced acute intolerance syndrome [see Warnings and Precautions (5.2)]
- Hypersensitivity reactions [see Warnings and Precautions (5.3)]
- Hepatic failure [see Warnings and Precautions (5.4)]
- Severe cutaneous adverse reactions [see Warnings and Precautions (5.5)]
- Photosensitivity [see Warnings and Precautions (5.6)]
- Nephrolithiasis [see Warnings and Precautions (5.7)]

The following adverse reactions have been identified from clinical studies or postmarketing reports of olsalazine. Because these reactions are reported voluntarily from a population of uncertain size, it is not always possible to reliably estimate their frequency or establish a causal relationship to drug exposure.

In double-blind, placebo- and active-controlled clinical trials of ulcerative colitis, discontinuations due to adverse reactions were reported in 10% of DIPENTUM-treated patients (N=441) and 7% of placebo-treated patients (N=208). Both sulfasalazine-tolerant and intolerant patients were included. The most common adverse reactions leading to discontinuation in DIPENTUM-treated patients were diarrhea/loose stools (6%), abdominal pain (1%), and rash/itching (1%).

In these controlled trials, adverse reactions reported in 1% or more of patients treated with DIPENTUM and greater than placebo are provided in Table 1.

Table 1 Adverse Reactions [reported in at least 1% of patients in the DIPENTUM group and greater than placebo] in Patients with Ulcerative Colitis in Double-Blind, Controlled Clinical Trials
Adverse Reaction | DIPENTUM (N=441) % | Placebo (N=208) %
Diarrhea | 11 | 7
Abdominal pain/cramps | 10 | 7
Nausea | 5 | 4
Arthralgia/Joint Pain | 4 | 3
Rash | 2 | 1
Upper Respiratory Infection | 2 | 0
Depression | 2 | 0
Vomiting | 1 | 0
Stomatitis | 1 | 0
Vertigo/Dizziness | 1 | 0
Itching | 1 | 0

Other adverse reactions reported in clinical trials or post-marketing experience:

Blood and Lymphatic System Disorders
aplastic anemia, anemia, eosinophilia, hemolytic anemia, leukopenia, lymphopenia, neutropenia, pancytopenia, reticulocytosis, thrombocytopenia

Cardiac Disorders
chest pains, heart block second degree, myocarditis, palpitations, pericarditis, peripheral edema, shortness of breath, tachycardia

A patient who developed thyroid disease 9 days after starting DIPENTUM was given propranolol and radioactive iodine and subsequently developed shortness of breath and nausea. The patient died 5 days later with signs and symptoms of acute diffuse myocarditis.

Ear and Labyrinth Disorders
tinnitus

Eye Disorders
dry eyes, vision blurred, watery eyes

Gastrointestinal Disorders
abdominal pain (upper), diarrhea with dehydration, dry mouth, epigastric discomfort, flare in symptoms, flatulence, increased blood in stool, pancreatitis, rectal bleeding, rectal discomfort

General Disorders and Administration Site Conditions
fever chills, hot flashes, irritability, pyrexia, rigors

Hepatobiliary Disorders
hepatic enzyme increased, hepatitis (including cholestasis, granulomatous, and non-specific, reactive), increased bilirubin

Reports of hepatotoxicity, including elevated liver function tests (SGOT/AST, SGPT/ALT, GGT, LDH, alkaline phosphatase, bilirubin), jaundice, cholestatic jaundice, cirrhosis, and possible hepatocellular damage including liver necrosis and liver failure. Some of these cases were fatal. One case of Kawasaki-like syndrome, which included hepatic function changes, was also reported.

Immune System Disorders
bronchospasm, erythema nodosum

Musculoskeletal and Connective Tissue Disorders
myalgia, muscle cramps

Nervous System Disorders
insomnia, paraesthesia, peripheral neuropathy, tremors

Psychiatric Disorders
mood swings

Renal and Urinary Disorders
dysuria, hematuria, interstitial nephritis, nephrolithiasis, nephrotic syndrome, proteinuria, urinary frequency

- Urine discoloration occurring ex-vivo caused by contact of mesalamine, including inactive metabolite, with surfaces or water treated with hypochlorite-containing bleach [see Warnings and Precautions (5.7)].

Reproductive System and Breast Disorders
impotence, menorrhagia, reversible oligospermia

Respiratory, Thoracic and Mediastinal Disorders
dyspnea, interstitial lung disease, pleurisy/pleuritis

Skin and Subcutaneous Tissue Disorders
AGEP, alopecia, angioneurotic edema, DRESS, erythema, photosensitivity reaction, SJS/TEN

Vascular Disorders
hypertension, orthostatic hypotension

7 DRUG INTERACTIONS

7.1 Nephrotoxic Agents, Including Non-Steroidal Anti-Inflammatory Drugs

The concurrent use of mesalamine with known nephrotoxic agents, including non‑steroidal anti‑inflammatory drugs (NSAIDs), may increase the risk of nephrotoxicity. Monitor patients taking nephrotoxic drugs for changes in renal function and mesalamine-related adverse reactions [see Warnings and Precautions (5.1)].

7.2 Azathioprine or 6-Mercaptopurine

The concurrent use of mesalamine with azathioprine or 6‑mercaptopurine and/or any other drugs known to cause myelotoxicity (e.g., thioguanine) may increase the risk for blood disorders, bone marrow failure, and associated complications. If concomitant use of DIPENTUM and azathioprine or 6-mercaptopurine cannot be avoided, monitor blood tests, including complete blood cell counts and platelet counts.

7.3 Low Molecular Weight Heparins or Heparinoids

The co-administration of salicylates and low molecular weight heparins or heparinoids may result in an increased risk of bleeding (i.e., hematomas) following neuraxial anesthesia. Discontinue DIPENTUM prior to the initiation of a low molecular weight heparin or heparinoid. If this is not possible, it is recommended to monitor patients closely for bleeding.

7.4 Varicella Vaccine

Avoid DIPENTUM, and other salicylates, for six weeks after the varicella vaccine to avoid a possible increased risk of developing Reye’s syndrome.

7.5 Interference With Urinary Normetanephrine Measurements

Use of DIPENTUM, which is converted to mesalamine, may lead to spuriously elevated test results when measuring urinary normetanephrine by liquid chromatography with electrochemical detection [see Warnings and Precautions (5.8)]. Consider an alternative, selective assay for normetanephrine.

8 USE IN SPECIFIC POPULATIONS

8.1 Pregnancy

Risk Summary

Published data from meta-analyses, cohort studies and case series on the use of mesalamine, the active moiety in DIPENTUM, during pregnancy have not reliably informed an association with mesalamine and major birth defects, miscarriage, or adverse maternal or fetal outcomes (see Data). There are adverse effects on maternal and fetal outcomes associated with ulcerative colitis in pregnancy (see Clinical Considerations). In animal reproduction studies, there were adverse developmental effects observed after oral administration of olsalazine sodium in pregnant rats during organogenesis at doses of 5 to 20 times the maximum recommended human dose (see Data).

The background risk of major birth defects and miscarriage for the indicated population is unknown. All pregnancies have a background risk of birth defect, loss, or other adverse outcomes. In the U.S. general population, the estimated background risk of major birth defects and miscarriage in clinically recognized pregnancies is 2% to 4% and 15% to 20%, respectively.

Clinical Considerations

Disease-associated maternal and embryo/fetal risk

Published data suggest that increased disease activity is associated with the risk of developing adverse pregnancy outcomes in women with ulcerative colitis. Adverse pregnancy outcomes include preterm delivery (before 37 weeks of gestation), low birth weight (less than 2500 g) infants, and small for gestational age at birth.

Data

Human Data

Published data from meta-analyses, cohort studies and case series on the use of mesalamine, the active moiety in DIPENTUM, during early pregnancy (first trimester) and throughout pregnancy have not reliably informed an association of mesalamine and major birth defects, miscarriage, or adverse maternal or fetal outcomes. There is no clear evidence that mesalamine exposure in early pregnancy is associated with an increased risk in major congenital malformations, including cardiac malformations. Published epidemiologic studies have important methodological limitations which hinder interpretation of the data, including inability to control for confounders, such as underlying maternal disease, and maternal use of concomitant medications, and missing information on the dose and duration of use for mesalamine products.

Animal Data

Olsalazine has been shown to produce adverse fetal developmental effects including reduced fetal weights, retarded ossifications, and immaturity of the fetal visceral organs when given during organogenesis to pregnant rats at doses of 100 to 400 mg/kg (5 to 20 times the maximum recommended human dose.

8.2 Lactation

Risk Summary

Data from published literature report the presence of mesalamine and its metabolite, N acetyl-5 aminosalicylic acid, in human milk in small amounts with relative infant doses (RID) of 0.1% or less for mesalamine (see Data). There are case reports of diarrhea in breastfed infants exposed to mesalamine (see Clinical Considerations). There is no information on the effects of the drug on milk production. The lack of clinical data during lactation precludes a clear determination of the risk of DIPENTUM to an infant during lactation; therefore, the developmental and health benefits of breastfeeding should be considered along with the mother’s clinical need for DIPENTUM and any potential adverse effects on the breastfed child from DIPENTUM or from the underlying maternal condition.

Clinical Considerations

Advise the caregiver to monitor the breastfed infant for diarrhea.

Data

In published lactation studies, maternal mesalamine doses from various oral and rectal mesalamine formulations and products ranged from 500 mg to 4.8 g daily. The average concentration of mesalamine in milk ranged from non-detectable to 0.5 mg/L. The average concentration of N-acetyl-5-aminosalicylic acid in milk ranged from 0.2 to 9.3 mg/L. Based on these concentrations obtained following administration of oral or rectal mesalamine, the active moiety of olsalazine, estimated infant daily dosages for an exclusively breastfed infant are 0 to 0.075 mg/kg/day (relative infant dose 0 to 0.1% of mesalamine and 0.03 to 1.4 mg/kg/day of N-acetyl-5-aminosalicylic acid).

Oral administration of olsalazine to lactating rats in doses 5 to 20 times the maximum recommended human dose produced growth retardation in the pups.

8.4 Pediatric Use

Safety and effectiveness in pediatric patients have not been established.

8.5 Geriatric Use

Clinical studies of DIPENTUM did not include sufficient numbers of subjects aged 65 and over to determine whether they respond differently from younger subjects. Reports from uncontrolled clinical studies and postmarketing reporting systems suggested a higher incidence of blood dyscrasias (i.e., agranulocytosis, neutropenia and pancytopenia) in patients receiving mesalamine-containing products such as DIPENTUM who were 65 years or older compared to younger adult patients, which may also be associated with ulcerative colitis, use of interacting drugs, or reduced renal function.

Consider monitoring of complete blood cell counts and platelet counts in patients 65 years and over during treatment with DIPENTUM. In general, consider the greater frequency of decreased hepatic, renal, or cardiac function, and of concurrent disease or other drug therapy in patients 65 years and over when prescribing DIPENTUM.

8.6 Renal Impairment

Mesalamine is known to be substantially excreted by the kidney, and the risk of adverse reactions to DIPENTUM, which is converted to mesalamine, may be greater in patients with impaired renal function. Evaluate renal function in all patients prior to initiation and periodically while on DIPENTUM therapy. Monitor patients with known renal impairment or history of renal disease or taking nephrotoxic drugs for decreased renal function and mesalamine-related adverse reactions. Discontinue DIPENTUM if renal function deteriorates while on therapy [see Warnings and Precautions (5.1)].

10 OVERDOSAGE

DIPENTUM is an aminosalicylate, and symptoms of salicylate toxicity include: nausea, vomiting and abdominal pain, tachypnea, hyperpnea, tinnitus, and neurologic symptoms (headache, dizziness, confusion, seizures). Severe salicylate intoxication may lead to electrolyte and blood pH imbalance and potentially to other organ (e.g., renal and liver) damage.

There is no specific antidote for olsalazine overdose; however, conventional therapy for salicylate toxicity may be beneficial in the event of acute overdosage and may include gastrointestinal tract decontamination to prevent of further absorption. Correct fluid and electrolyte imbalance by the administration of appropriate intravenous therapy and maintain adequate renal function.

11 DESCRIPTION

The active ingredient in DIPENTUM (olsalazine sodium) is the sodium salt of a salicylate, disodium 3,3'-azobis (6-hydroxybenzoate) a compound that is effectively bioconverted to mesalamine (5-aminosalicylic acid,5-ASA), an aminosalicylate. Its empirical formula is C14H8N2Na2O6 with a molecular weight of 346.21.

The structural formula is:

Olsalazine sodium is a yellow crystalline powder, which melts with decomposition at 240°C. It is the sodium salt of a weak acid, soluble in water and DMSO, and practically insoluble in ethanol, chloroform, and ether. Olsalazine sodium has acceptable stability under acidic or basic conditions.

DIPENTUM is supplied in capsules for oral administration. Each DIPENTUM hard gelatin capsule contains 250 mg olsalazine sodium (equivalent to 233.4 mg of olsalazine). The inert ingredient in each capsule is magnesium stearate. The capsule shell contains the following inactive ingredients: black iron oxide, caramel, gelatin, and titanium dioxide.

12 CLINICAL PHARMACOLOGY

12.1 Mechanism of Action

Upon reaching the colon, colonic bacteria convert olsalazine into 5‑aminosalicylic acid (5-ASA or mesalazine). The mechanism of action of 5-ASA (mesalamine) is not fully understood, but appears to be a topical anti-inflammatory effect on colonic epithelial cells. Mucosal production of arachidonic acid metabolites, both through the cyclooxygenase pathways (i.e., prostanoids) and through the lipoxygenase pathways (i.e., leukotrienes and hydroxyeicosatetraenoic acids) is increased in patients with ulcerative colitis, and it is possible that mesalamine diminishes inflammation by blocking cyclooxygenase and inhibiting prostaglandin production in the colon.

12.2 Pharmacodynamics

The exposure-response relationship and time course of pharmacodynamic response for the safety and effectiveness of mesalamine have not been fully characterized.

12.3 Pharmacokinetics

Olsalazine

The usual dose of sulfasalazine for maintenance of remission in patients with ulcerative colitis is 2 grams daily, which would provide approximately 0.8 gram of mesalamine to the colon. More than 0.9 gram of mesalamine would usually be made available in the colon from 1 gram of olsalazine. Patients on daily doses of 1 g olsalazine for 2 to 4 years show a stable plasma concentration of olsalazine-S (3.3 to 12.4 micromol/L).

Absorption

Based on oral and intravenous dosing studies, approximately 2.4% of a single 1 g oral dose is absorbed. Following oral administration of olsalazine, the 98 to 99% of a dose will reach the colon, where each molecule is rapidly converted into two molecules of 5‑ aminosalicylic acid (5-ASA) by colonic bacteria and the low prevailing redox potential found in this environment. The liberated 5-ASA is absorbed slowly resulting in very high local concentrations in the colon. The pharmacokinetics of olsalazine are similar in both healthy volunteers and in patients with ulcerative colitis. Maximum serum concentrations of olsalazine appear after approximately 1 hour and, even after a 1 g single dose, are low (e.g., 1.6 to 6.2 micromol/L).

Distribution

Olsalazine is more than 99% bound to plasma proteins. It does not interfere with protein binding of warfarin. Olsalazine-O-sulfate (olsalazine-S) is more than 99% bound to plasma proteins. Less than 1% of both olsalazine and olsalazine-S appears undissociated in plasma.

Elimination

Metabolism

The conversion of olsalazine to mesalamine (5-ASA) in the colon is similar to that of sulfasalazine, which is converted into sulfapyridine and mesalamine.

Approximately 0.1% of an oral dose of olsalazine is metabolized in the liver to olsalazine-S.

Excretion

Olsalazine has a very short serum half-life, approximately 0.9 hour. The urinary recovery of olsalazine is below 1%. Total recovery of oral 14C-labeled olsalazine in humans ranges from 90 to 97%.

5-aminosalicylic acid (5-ASA)

Absorption

Serum concentrations of 5-ASA are detected after 4 to 8 hours. The peak levels of 5-ASA after an oral dose of 1 g olsalazine range from 0 to 4.3 micromol/L. No accumulation of 5-ASA or Ac-5-ASA (the major metabolite of 5-ASA) in plasma has been detected.

Distribution

5-ASA and Ac-5-ASA are 74 and 81%, respectively, bound to plasma proteins.

Elimination

Metabolism

N-acetyl-5-ASA (Ac-5-ASA), the major metabolite of 5-ASA found in plasma and urine, is acetylated (deactivated) in at least two sites, the colonic epithelium and the liver. Ac-5-ASA is found in the serum, with peak values of 1.7 to 8.7 micromol/L after a single 1.0 g dose. Pharmacological activities of Ac-5-ASA are unknown.

Excretion

Approximately 20% of the total 5-ASA is recovered in the urine, where it is found almost exclusively as Ac-5-ASA. Of the total 5-ASA found in the urine, more than 90% is in the form of Ac-5-ASA. Only small amounts of 5-ASA are detected. The remaining 5-ASA is partially acetylated and is excreted in the feces. From fecal dialysis, the concentration of 5-ASA in the colon following olsalazine has been calculated to be 18 to 49 micromol/L.

13 NONCLINICAL TOXICOLOGY

13.1 Carcinogenesis, Mutagenesis, Impairment of Fertility

Carcinogenesis

In a two year oral carcinogenicity study in rats, olsalazine was administered to male and female Wistar rats at daily doses of 200, 400, and 800 mg/kg/day (approximately 10 to 40 times the maximum human recommended dose, based on a patient weight of 50 kg and a human dose of 1 g). Urinary bladder transitional cell carcinomas were found in three male rats receiving 40 times the human dose and were not found in untreated male controls. In the same study, urinary bladder transitional cell carcinoma and papilloma occurred in 2 untreated control female rats (2%). No such tumors were found in any of the female rats treated at doses up to 40 times the maximum recommended human dose.

In an eighteen-month oral carcinogenicity study in mice, olsalazine was administered to male and female CD-1 mice at daily doses of 500, 1000, and 2000 mg/kg/day (approximately 25 to 100 times the maximum recommended human dose). Liver hemangiosarcomas were found in two male mice (4%) receiving olsalazine at 100 times the maximum recommended human dose, while no such tumor occurred in the other treated male mice groups or any of the treated female mice. The observed incidence of this tumor is within the 4% incidence in historical controls.

Mutagenesis

Olsalazine was not mutagenic in the in vitro Ames test, mouse lymphoma cell mutation assay, human lymphocyte chromosomal aberration test, or the in vivo rat bone marrow cell chromosomal aberration test.

Impairment of Fertility

Olsalazine in a dose range of 100 to 400 mg/kg/day (approximately 5 to 20 times the maximum recommended human dose) did not influence the fertility of male or female rats.

13.2 Animal Toxicology and/or Pharmacology

Preclinical subacute and chronic toxicity studies in rats have shown the kidney to be the major target organ of olsalazine toxicity. At an oral daily dose of 400 mg/kg or higher, olsalazine treatment produced nephritis and tubular necrosis in a 4-week study; interstitial nephritis and tubular calcinosis in a 6-month study, and renal fibrosis, mineralization, and transitional cell hyperplasia in a 1-year study.

14 CLINICAL STUDIES

Two double-blind controlled trials have demonstrated the efficacy of DIPENTUM as maintenance therapy in patients with ulcerative colitis. In the first trial, patients with ulcerative colitis in remission were randomized to DIPTENUM 500 mg twice daily or placebo, and relapse rates for a six month period of time were compared. For the 52 patients randomized to DIPENTUM, 12 relapses occurred, while for the 49 patients randomized to placebo, 22 relapses occurred. This difference in relapse rates was significant (p<0.02).

In the second trial, 164 patients with ulcerative colitis in remission were randomized to DIPENTUM 500 mg twice daily or sulfasalazine 1 gram twice daily, and relapse rates were compared after six months. The relapse rate for DIPENTUM-treated patients was 19.5% and 12.2% for sulfasalazine-treated patients, a non-significant difference.

16 HOW SUPPLIED/STORAGE AND HANDLING

DIPENTUM is supplied as beige colored capsules, containing 250 mg olsalazine sodium imprinted with “DIPENTUM® 250 mg” on the capsule shell, available as:

Bottles of 100’s NDC 0037-6860-10

Store at 20°C to 25°C (68°F to 77°F). Excursions permitted to 15°C to 30°C (59°F to 86°F) [see USP Controlled Room Temperature].

17 PATIENT COUNSELING INFORMATION

Renal Impairment

Inform patients that DIPENTUM may decrease their renal function, especially if they have known renal impairment or are taking nephrotoxic drugs, and periodic monitoring of renal function will be performed while they are on therapy. Advise patients to complete all blood tests ordered by their healthcare provider [see Warnings and Precautions (5.1)].

Mesalamine-Induced Acute Intolerance Syndrome and Other Hypersensitivity Reactions

Instruct patients to stop taking DIPENTUM and report to their healthcare provider if they experience new or worsening symptoms of acute intolerance syndrome (cramping, abdominal pain, bloody diarrhea, fever, headache, and rash) or other symptoms suggestive of mesalamine-induced hypersensitivity [see Warnings and Precautions (5.2, 5.3)].

Hepatic Failure

Advise patients with known liver disease to contact their healthcare provider if they experience signs or symptoms of worsening liver function [see Warnings and Precautions (5.4)].

Severe Cutaneous Adverse Reactions

Inform patients of the signs and symptoms of severe cutaneous adverse reactions. Instruct patients to stop taking DIPENTUM and report to their healthcare provider at first appearance of a severe cutaneous adverse reaction or other sign of hypersensitivity [see Warnings and Precautions (5.5)].

Photosensitivity

Advise patients with pre-existing skin conditions to avoid sun exposure, wear protective clothing, and use a broad-spectrum sunscreen when outdoors [see Warnings and Precautions (5.6)].

Nephrolithiasis

Instruct patients to drink an adequate amount of fluids during treatment in order to minimize the risk of kidney stone formation and to contact their healthcare provider if they experience signs or symptoms of a kidney stone (e.g., severe side or back pain, blood in the urine) [see Warnings and Precautions (5.7)].

Blood Disorders

Inform elderly patients and those taking azathioprine or 6-mercaptopurine of the risk for blood disorders and the need for periodic monitoring of complete blood cell counts and platelet counts while on therapy. Advise patients to complete all blood tests ordered by their healthcare provider [see Drug Interactions (7.2), Use in Specific Populations (8.5)].

Administration

- Instruct patients to drink an adequate amount of fluids during treatment.
- Advise patients that urine may become discolored reddish-brown while taking DIPENTUM when it comes in contact with surfaces or water treated with hypochlorite-containing bleach. If discolored urine is observed, advise patients to observe their urine flow. Report to the healthcare provider only if urine is discolored on leaving the body, before contact with any surface or water (e.g., in the toilet) [see Dosage and Administration (2)].

Manufactured for:
MEDA
PHARMACEUTICALS
Canonsburg, PA 15317 U.S.A.

Manufactured by:
SOCIETAL™
CDMO
Societal CDMO Gainesville, LLC
Gainesville, GA 30504, USA

© 2024 Viatris Inc.

DIPENTUM is a registered trademark of Alaven Pharmaceutical LLC, a Viatris Company.

Rev. 7/2024
IN-686010-08

PRINCIPAL DISPLAY PANEL – 250 mg

NDC 0037-6860-10

Dipentum®
(olsalazine sodium)
capsule, gelatin coated

250 mg

Rx only

100 Capsules

USUAL DOSAGE: See package circular
for complete product information.

PHARMACIST: Dispense in a
well-closed container.

Store at 25°C (77°F); excursions
15°-30°C (59°-86°F).

Manufactured for:
MEDA
PHARMACEUTICALS®
Canonsburg, PA 15317 U.S.A.

Manufactured by:
Societal CDMO Gainesville, LLC
Gainesville, GA 30504, USA

©2023 Viatris Inc.

DIPENTUM is a registered trademark
of Alaven Pharmaceutical LLC,
a Viatris Company.

LB-686010-05
6003065-04